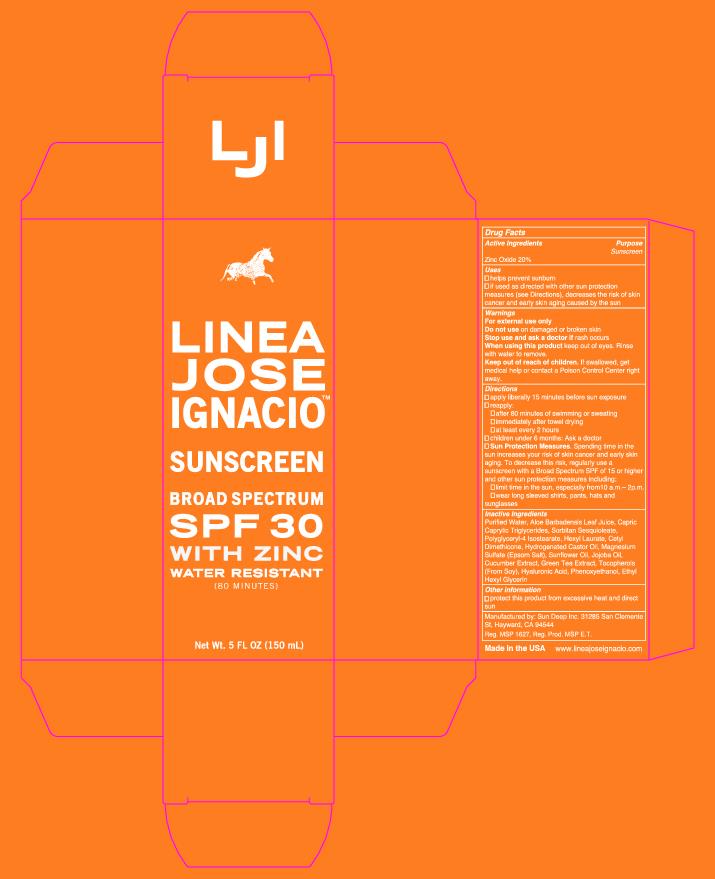 DRUG LABEL: Linea Jose Ignacio Sunscreen Broad Spectrum SPF 30 with Zinc
NDC: 69096-8002 | Form: LOTION
Manufacturer: Linea Jose Ignacio LLC
Category: otc | Type: HUMAN OTC DRUG LABEL
Date: 20181001

ACTIVE INGREDIENTS: ZINC OXIDE 30 g/150 g
INACTIVE INGREDIENTS: PHENOXYETHANOL; CAPRIC ACID; SORBITAN SESQUIOLEATE; POLYGLYCERYL-4 ISOSTEARATE; CETYL DIMETHICONE 150; HYDROGENATED CASTOR OIL; MAGNESIUM ASCORBYL PHOSPHATE; SUNFLOWER OIL; JOJOBA OIL; CUCUMBER FRUIT OIL; GREEN TEA LEAF; TOCOPHEROL; HYALURONIC ACID; ETHYLHEXYL LAURATE; WATER; ETHYLHEXYLGLYCERIN; ALOE VERA LEAF

Broad Spectrum Sunscreen SFP 30 with Zinc
Water Resistant (80 Minutes)

Broad Spectrum Sunscreen SFP 30 with Zinc Water Resistant (80 Minutes)

Drug Facts

Active Ingredients Purpose

Sunscreen

Zinc Oxide 20%

Uses

■ helps prevent sunburn

■ if used as directed with other sun protection measures (see Directions), decreases the risk of skin cancer and early skin aging caused by the sun

Warnings

For external use only

Do not use on damaged or broken skin

Stop use and ask a doctor if rash occurs

When using this product keep out of eyes. Rinse with water to remove.

Keep out of reach of children. If swallowed, get medical help or contact a Poison Control Center right away.

Directions

■ apply liberally 15 minutes before sun exposure

■ reapply:

■ after 80 minutes of swimming or sweating

■ immediately after towel drying

■ at least every 2 hours

■ children under 6 months: Ask a doctor

■ Sun Protection Measures. Spending time in the sun increases your risk of skin cancer and early skin aging. To decrease this risk, regularly use a sunscreen with a Broad Spectrum SPF of 15 or higher and other sun protection measures including:

■ limit time in the sun, especially from 10 a.m. – 2 p.m.

■ wear long sleeved shirts, pants, hats and sunglasses

Inactive Ingredients

Purified Water, Aloe Barbadensis Leaf Juice, Capric Caprylic Triglycerides,

Sorbitan Sesquioleate, Polyglyceryl-4 Isostearate, Hexyl Laurate, Cetyl Dimethicone, Hydrogenated Castor Oil, Magnesium Sulfate (Epsom Salt), Sunflower Oil, Jojoba Oil, Cucumber Extract, Green Tea Extract, Tocopherols (From Soy), Hyaluronic Acid, Phenoxyethanol, Ethyl Hexyl Glycerin

Other information

■ protect this product from excessive heat and direct sun

Manufactured by: Sun Deep Inc. 31285 San Clemente St, Hayward, CA 94544

Made in the USA www.lineajoseignacio.com